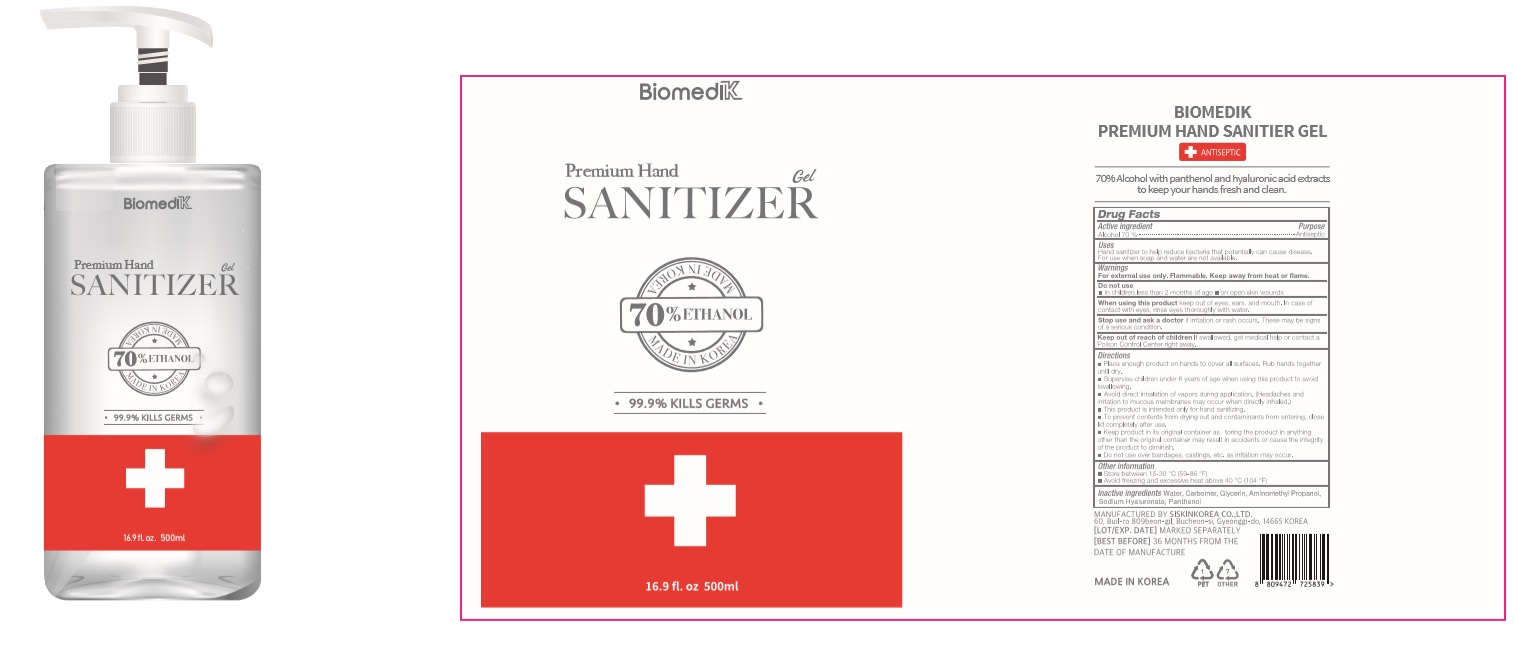 DRUG LABEL: BIOMEDIK Premium HAND SANITIZER Gel
NDC: 74514-5570 | Form: GEL
Manufacturer: SISKINKOREA CO.,LTD.
Category: otc | Type: HUMAN OTC DRUG LABEL
Date: 20200527

ACTIVE INGREDIENTS: ALCOHOL 350 mL/500 mL
INACTIVE INGREDIENTS: GLYCERIN; AMINOMETHYLPROPANOL; PANTHENOL; WATER; HYALURONATE SODIUM; CARBOMER HOMOPOLYMER, UNSPECIFIED TYPE

BIOMEDIK Premium Hand Sanitizer Gel [74514-5570-1] 500 mL, Bottle+Pump